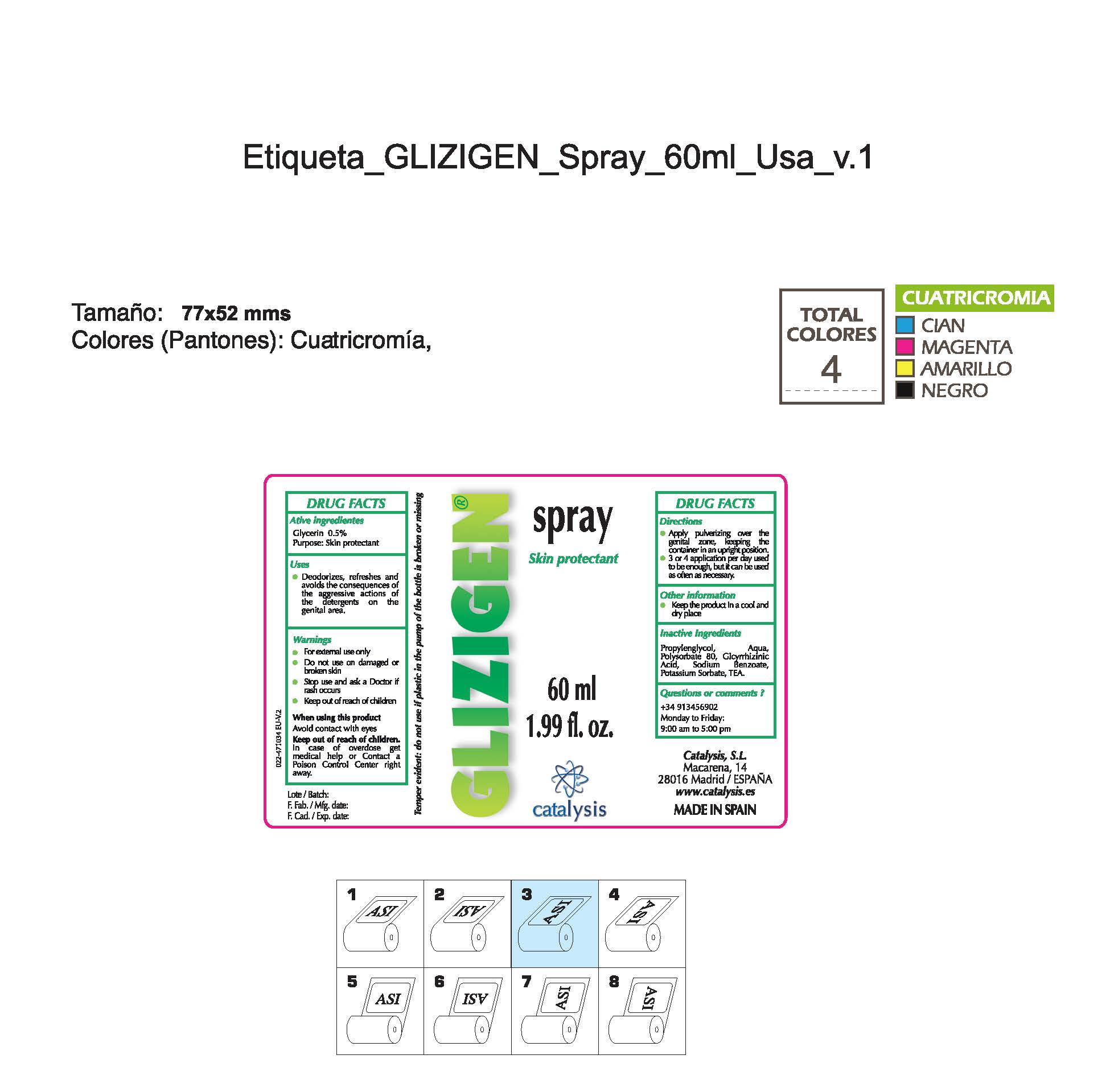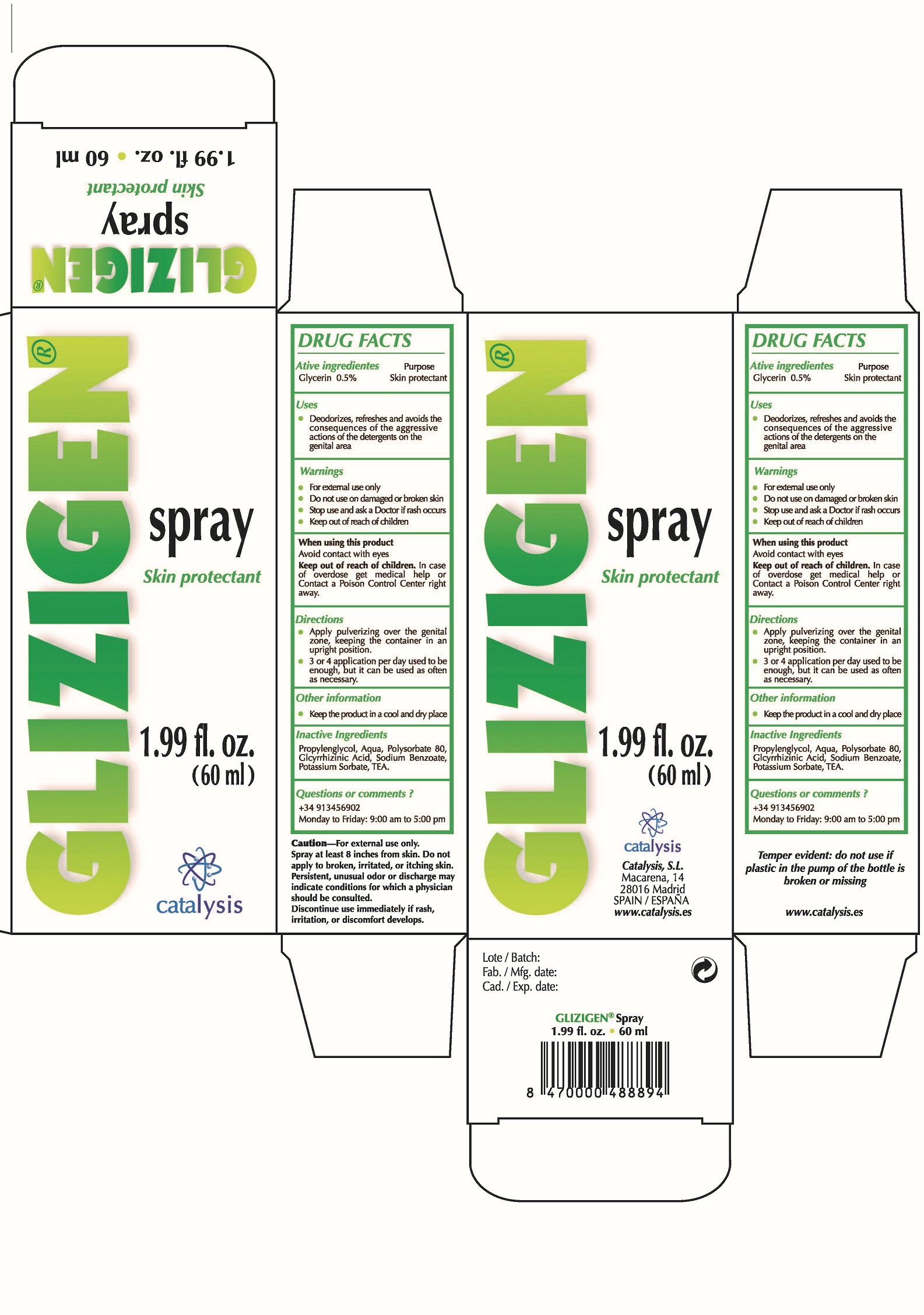 DRUG LABEL: Glizigen Skin Protectant
NDC: 64539-018 | Form: SPRAY
Manufacturer: Catalysis, SL
Category: otc | Type: HUMAN OTC DRUG LABEL
Date: 20180322

ACTIVE INGREDIENTS: GLYCERIN 0.5 mg/1 mL
INACTIVE INGREDIENTS: POLYSORBATE 80 0.8 mg/1 mL; SODIUM BENZOATE 0.1 mg/1 mL; POTASSIUM SORBATE 0.1 mg/1 mL; WATER 100 mg/1 mL; PROPANEDIOL 50 mg/1 mL; TEA LEAF 0.1 mg/1 mL; GLYCYRRHIZIN 0.1 mg/1 mL

ACTIVE INGREDIENT

Glycerin 0.5%................Skin Protectant

- Stop use and ask a doctor if rash occurs
- Children under 6 months: ask a doctor

- Do not use on damaged or broken skin.

- Keep out of reach of children

WARNINGS

- For external use only.
- Do not use on damaged or broken skin.
- When using this product keep our of the eyes. Rinse with water to remove.
- Stop use and ask a doctor if rash occurs.
- Keep out of reach of children
- Children under 6 months: as a doctor

QUESTIONS

- + 34 913456902 M-F 9:00 am to 5:00 pm

INDICATIONS AND USAGE

- deodorizes, refreshes and avoids the consequences of the agressive actions of the detergents in the genital areas

DOSAGE AND ADMINISTRATION

- apply pulverizing over the genital zone keeping the container in an upright position
- 3 or 4 applications per day used to be anough, but it can be used as often as necessary

PURPOSE

- apply pulverizing over the genital zone keeping the container in an upright position
- 3 or 4 applications per day used to be anough, but it can be used as often as necessary

INACTIVE INGREDIENT

Propyleneglycol, water, Polysorbate 80, Glycyrrhizinic Acid, Sodium Benzoate, Potassium Sorbate, TEA